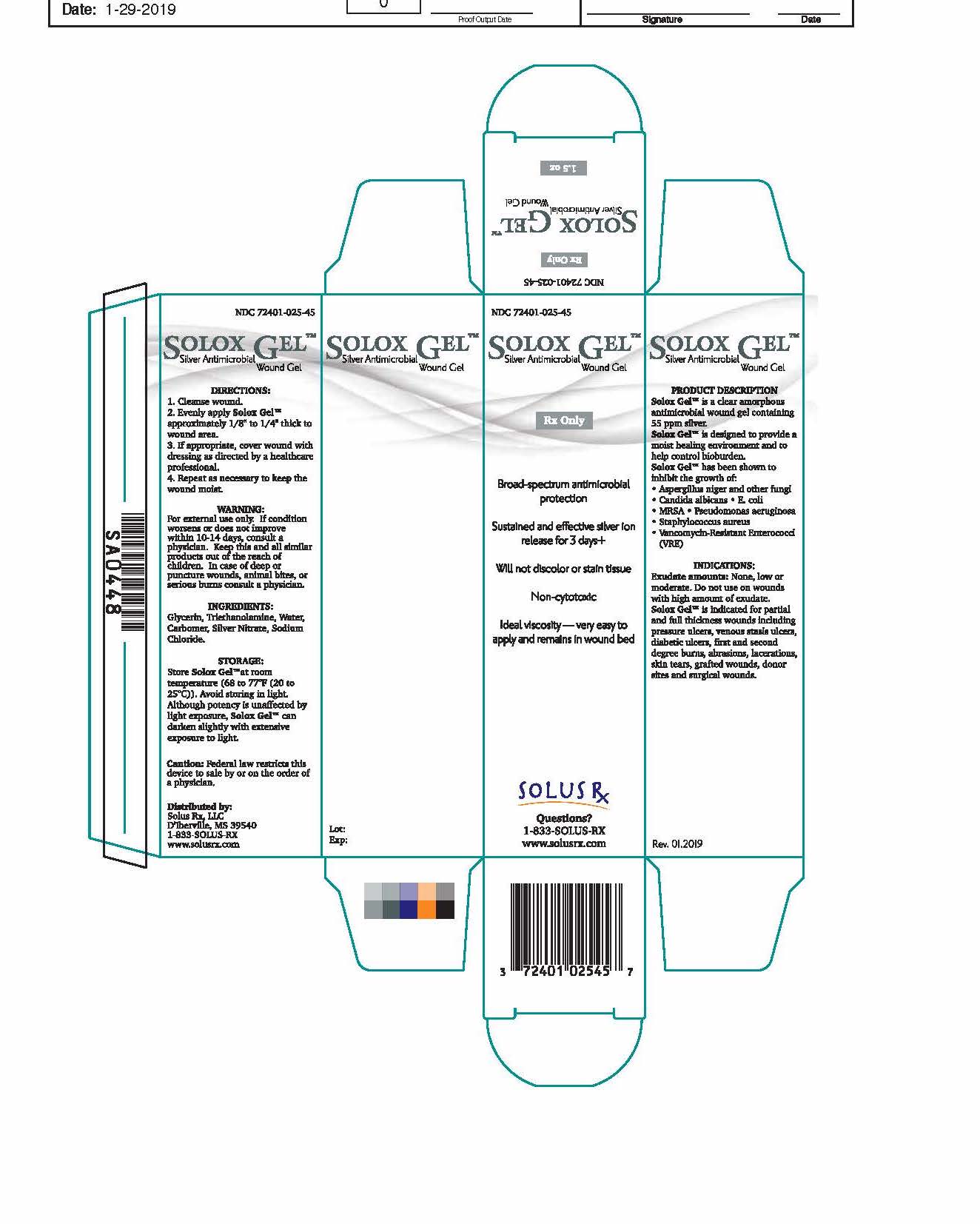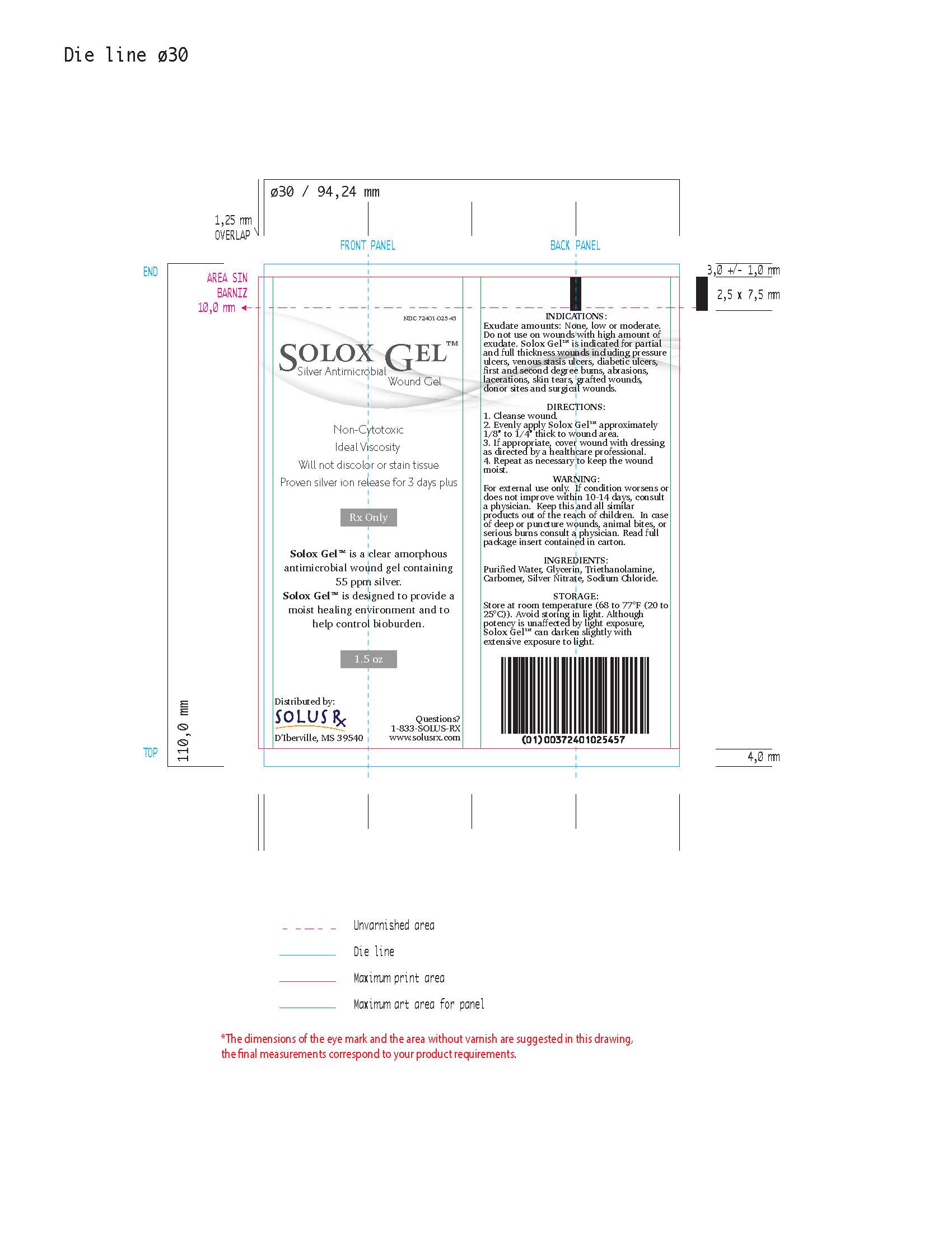 DRUG LABEL: Solox Gel
NDC: 72401-025
Manufacturer: Solus Rx, LLC
Category: other | Type: PRESCRIPTION MEDICAL DEVICE LABEL
Date: 20190206

Solox Gel - Silver Antimicrobial Wound Gel

PRODUCT DESCRIPTION

Solox Gel™ is a clear amorphous prescription antimicrobial wound gel containing 55 ppm silver. Solox Gel™ is designed to provide a moist healing environment and to help control bioburden.

Solox Gel™ has been shown to inhibit the growth of: • Aspergillus niger and other fungi • Candida albicans • E. coli • MRSA • Pseudomonas aeruginosa • Staphylococcus aureus • Vancomycin-Resistant Enterococci (VRE)

INDICATIONS

Exudate amounts: None, low or moderate. Do not use on wounds with highamount of exudate.
Solox Gel™ is indicated for partial and full thickness wounds including pressure ulcers, venous stasis ulcers, diabetic ulcers, first and second degree bums, abrasions, lacerations, skin tears, grafted wounds, donor sites and surgical wounds.

CONTRAINDICATIONS

Solox Gel™ is contraindicated to persons with allergies to any of the ingredients.

ADVERSE REACTIONS

There are no known side effects or adverse reactions.

INSTRUCTIONS

DIRECTIONS:
1. Cleanse wound.
2. Evenly apply Solox Gel™ approximately 1/8” to 1/4” thick to wound area.
3. If appropriate, cover wound with dressing as directed by a healthcare professional.
4. Repeat as necessary to keep the wound moist.

CHANGING THE DRESSING:
1. Remove secondary dressing, if one is applied.
2. Cleanse the wound bed to remove any remaining Solox Gel™.
3. Re-apply Solox Gel™, following the directions.

WARNING

For external use only. If condition worsens or does not improve within 10-14 days, consult a physician. Keep this and all similar products out of the reach of children. In case of deep or puncture wounds, animal bites, or serious burns consult a physician.

STORAGE

Store Solox Gel™ at room temperature (68 to 77°F (20 to 25°C)). Avoid storing in light. Although potency is unaffected by light exposure, Solox Gel™ can darken slightly with extensive exposure to light.

HOW SUPPLIED

Solox Gel™ is supplied in a 1.5 oz. tube, NDC 72401-025-45. RX ONLY.

Made in the USA.

Distributed by:

Solus Rx, LLC

D'Iberville, MS 39540